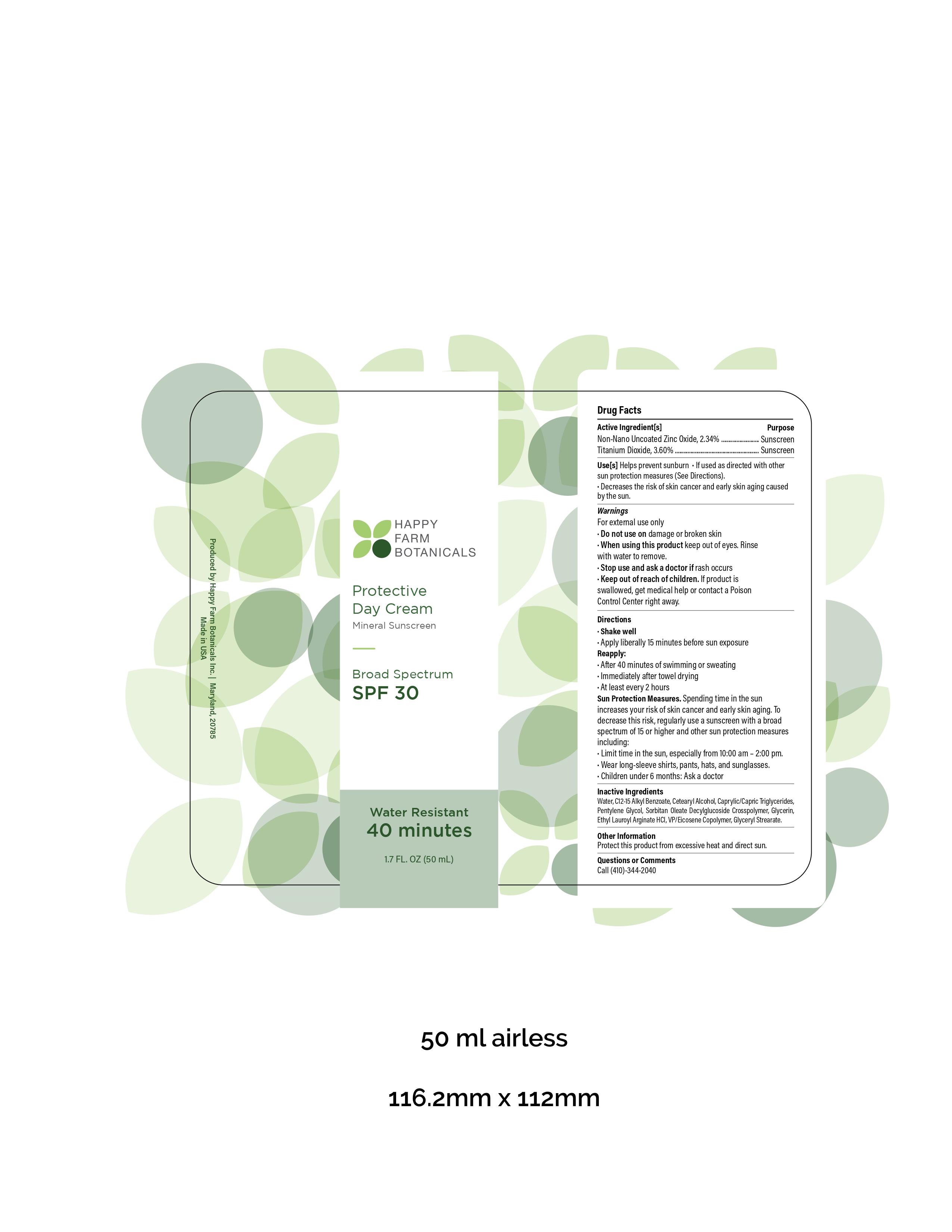 DRUG LABEL: Happy Farm Botanicals Protective Day Cream SPF 30
NDC: 73964-030 | Form: CREAM
Manufacturer: Happy Farm Botanicals, Inc.
Category: otc | Type: HUMAN OTC DRUG LABEL
Date: 20220209

ACTIVE INGREDIENTS: ZINC OXIDE 2.34 g/100 g; TITANIUM DIOXIDE 3.6 g/100 g
INACTIVE INGREDIENTS: GLYCERYL STEARATE SE 1 g/100 g; CETOSTEARYL ALCOHOL 4 g/100 g; MEDIUM-CHAIN TRIGLYCERIDES 4 g/100 g; EICOSYL POVIDONE (2 EICOSYL BRANCHES/REPEAT) 2 g/100 g; PENTYLENE GLYCOL 4 g/100 g; C12-15 ALKYL ETHYLHEXANOATE 5 g/100 g; WATER 65.06 g/100 g; SORBETH-12/OLEATE/DIMER DILINOLEATE CROSSPOLYMER 4 g/100 g; XANTHAN GUM 1 g/100 g; ETHYL LAUROYL ARGINATE HYDROCHLORIDE 2 g/100 g; GLYCERIN 2 g/100 g

Sunscreen Product Listing

Active Ingredients Section

Active Ingredients

Non-Nano Uncoated Zinc Oxide, 2.34%

Titanium Dioxide, 3.60%

Purpose

Sunscreen

Uses

Helps prevent sunburn
If used as directed with other sun protection measures (See Directions).

Decreases the risk of skin cancer and early skin aging caused by the sun.

Warnings

For external use only

Do not use on damage or broken skin.

Do not use on damage or broken skin

When using this product keep out of eyes. Rinse with water to remove.

Stop use and ask a doctor if rash occurs.

Keep out of reach of Children. If product is swallowed get medical help or contact a poison control center right away.

Directions

- Shake well
- Apply liberally 15 minutes before sun exposure
- Reapply:
- After 40 minutes of swimming or sweating
- Immediately after towel drying
- at least every 2 hours
- Sun Protection Measures. Spending time in the sun increases your risk of skin cancer and early skin aging. To decrease this risk, regularly use a sunscreen with a broad spectrum of 15 or higher and other sun protection measures including:
- Limit time in the sun, especially from 10:00 am – 2:00 pm.\
- Wear long-sleeve shirts, pants, hats, and sunglasses.
- Children under 6 months: Ask a doctor

Other Information

- Protect this product from excessive heat and direct sun.

Inactive Ingredients

Water, C12-15 Alkyl Benzoate, Cetearyl Alcohol, Caprylic/Capric Triglycerides, Pentylene Glycol, Sorbitan Oleate Decylglucoside Crosspolymer, Glycerin, Ethyl Lauroyl Arginate HCl, VP/Eicosene Copolymer, Glyceryl Strearate.